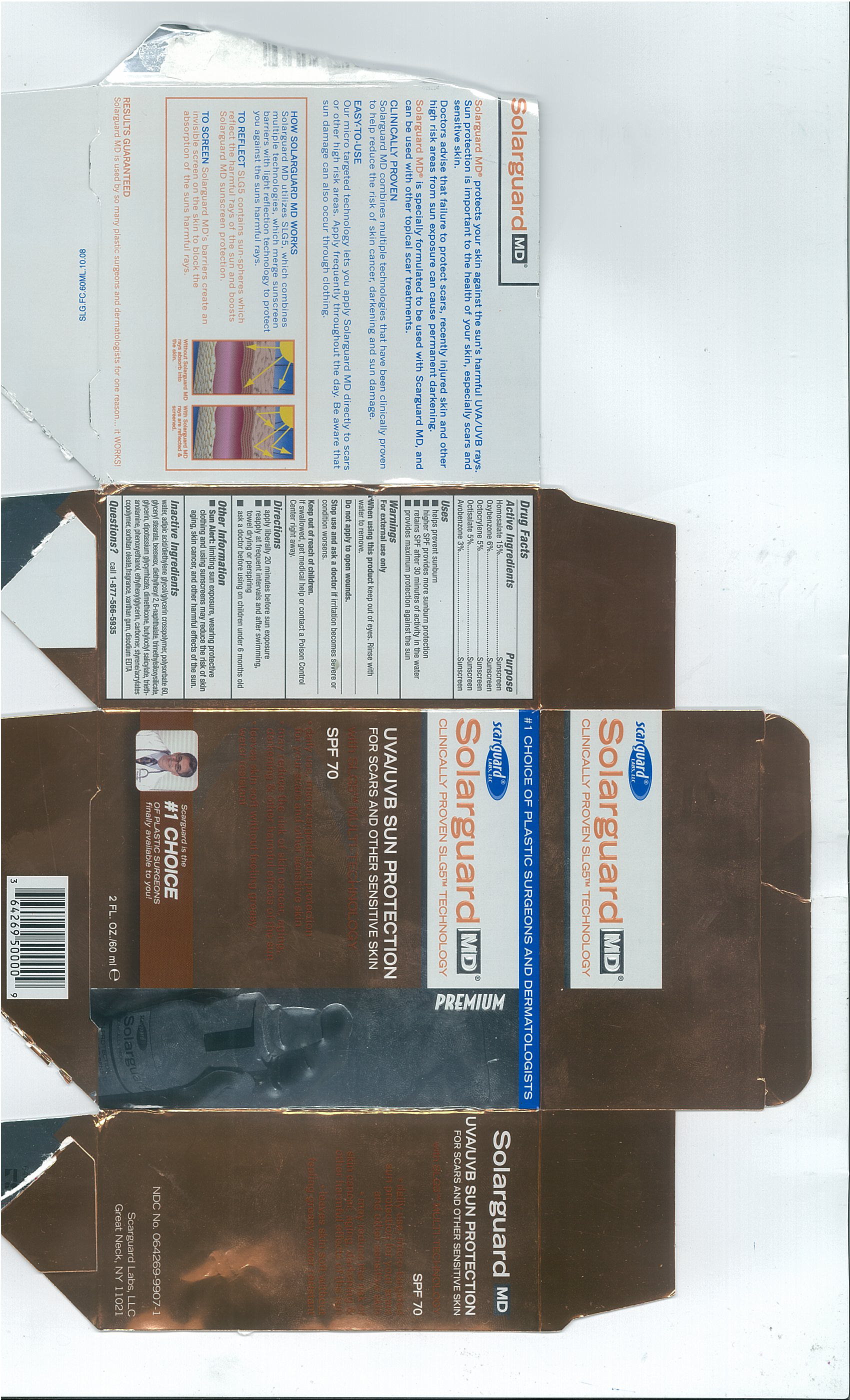 DRUG LABEL: Solarguard MD
NDC: 64269-9907 | Form: SPRAY
Manufacturer: Scarguard Labs, LLC
Category: otc | Type: HUMAN OTC DRUG LABEL
Date: 20100610

ACTIVE INGREDIENTS: Homosalate 15 mL/100 mL; Oxybenzone 6 g/100 mL; Octocrylene 5 mL/100 mL; Octisalate 5 mL/100 mL; Avobenzone 3 g/100 mL
INACTIVE INGREDIENTS: WATER; Polysorbate 60; GLYCERYL MONOSTEARATE; YELLOW WAX; GLYCERIN; Glycyrrhizinate Dipotassium; Dimethicone; TROLAMINE; Phenoxyethanol; CARBOMER HOMOPOLYMER TYPE C; SORBITAN MONOOLEATE; XANTHAN GUM; EDETATE DISODIUM; ETHYLHEXYLGLYCERIN

Drug Facts

Active Ingredients

Homosalate 15%
Oxybenzone 6%
Octocrylene 5%
Octisalate 5%
Avobenzone 3%

Purpose

Sunscreen
Sunscreen
Sunscreen
Sunscreen
Sunscreen

Uses

- helps prevent sunburn
- high SPF provides more sunburn protection
- retains SPF after 30 minutes of activity in the water
- provides maximum protection against the sun

Warnings

For external use only

When using this product keep out of eyes. Rinse with water to remove.

Do not apply to open wounds.

Stop use and ask a doctor if irritation becomes severe or condition worsens.

Keep out of reach of children

If swallowed, get medical help or contact a Poison Control
Center right away.

Directions

- apply liberally 20 minutes before sun exposure
- reapply at frequent intervals and after swimming, towel drying or perspiring
- ask a doctor before using on children under 6 months old

Other Information

- Sun Alert: limiting sun exposure, wearing protective clothing and using sunscreens may reduce the risk of skin aging, skin cancer, and other harmful effects of the sun.

Inactive Ingredients

water, adipic acid/diethylene glycol/glycerin crosspolymer, polysorbate 60, glyceryl stearate, beeswax, diethylhexyl 2,6-naphthalate, trimethylsiloxysilicate,glycerin, dipotassium glycyrrhizate, dimethicone, butyoctyl salicylate, triethanolamine, phenoxyethanol ethylhexylgylcerin, carbomer, styrene/acrylates copolymer, sorbitan oleate, fragrance, xanthan gum, disodium EDTA

Questions?

call 1-877-566-5935